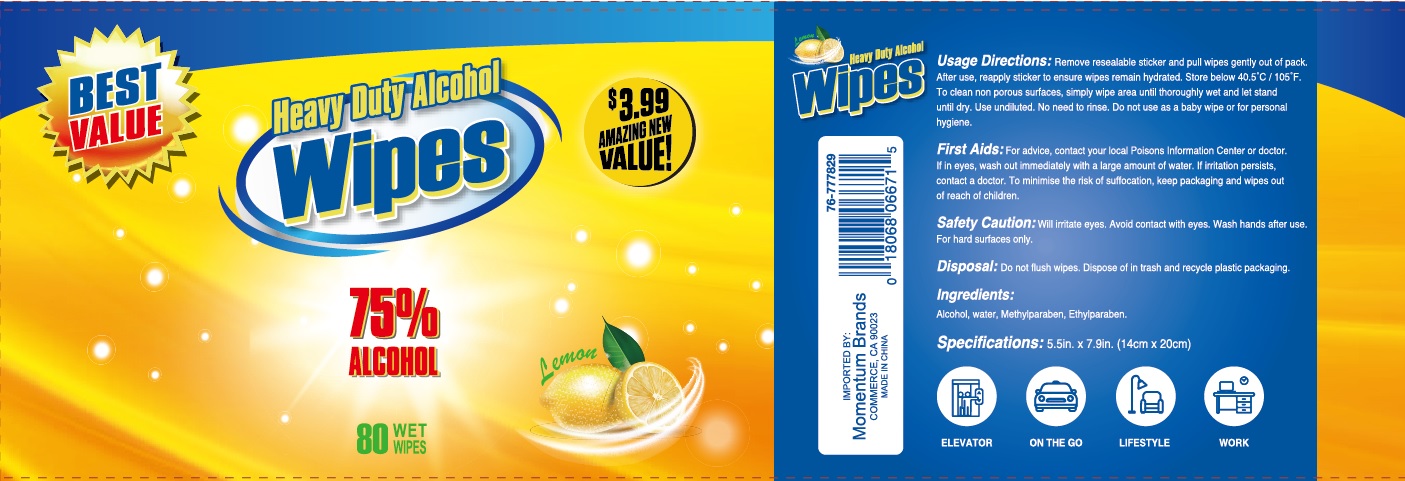 DRUG LABEL: Heavy Duty Alcohol Wipes
NDC: 42129-118 | Form: CLOTH
Manufacturer: Fustin(Xiamen) Commodity Co., ltd
Category: otc | Type: HUMAN OTC DRUG LABEL
Date: 20210226

ACTIVE INGREDIENTS: ALCOHOL 75 1/100 1
INACTIVE INGREDIENTS: WATER; METHYLPARABEN; ETHYLPARABEN

Alcohol wipes

Active Ingredient

Alcohol 75%

Purpose

Antiseptic

Warnings

For external use only.
Flammable. Keep away from fire or flame.
When using this product Will irritate eyes. Avoid contact with eyes. Wash hands afer use. For hand surfaces only.

First Adis: For advise, contact your local Poisons information Center or doctor. If in eyes, wash out immediately with a large amount of water. If irritation persists, contact a doctor. To minimise the risk of suffocation, keep packaging and wipes out of reach of children.

INDICATIONS AND USAGE

Decrease bacteria on hands

Keep out of reach of children. If swallowed, get medical help or contact a Poison Control Center right away.

Directions

Remove resealable sticker and pull wipes gently out of pack. After use, reapply sticker to ensure wipes remain hydrated. Store below 40.5 ℃/105℉.

To clean non porous surfaces, simpjy wipe area until thoroughly wet and let stand until dry. Use unfiluted. No need to rinse. Do not use as a baby wipe or for perseonal hygiene.

Inactive ingredients

Water, Methylparaben, Ethylparaben